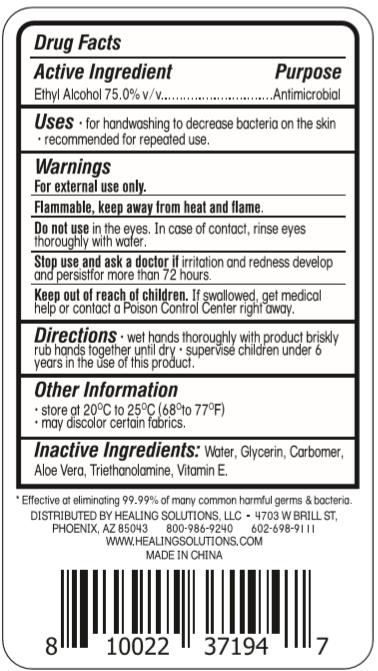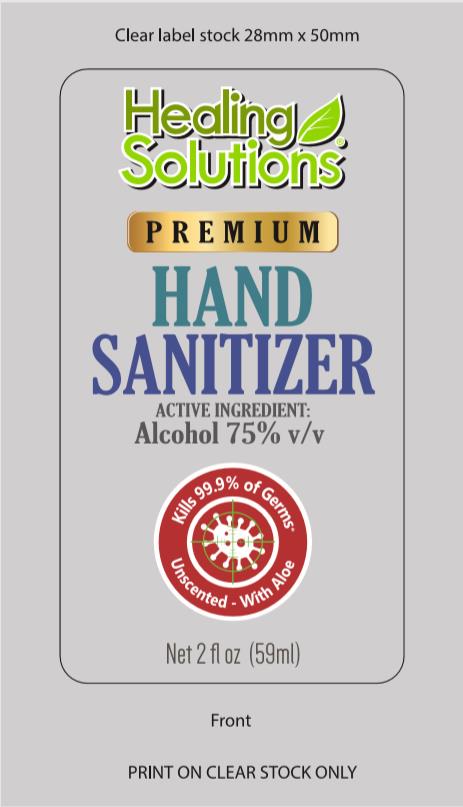 DRUG LABEL: Healing Solutions
NDC: 75742-007 | Form: GEL
Manufacturer: Zhejiang Guoyao Jingyue Aerosol Co., Ltd.
Category: otc | Type: HUMAN OTC DRUG LABEL
Date: 20260105

ACTIVE INGREDIENTS: ALCOHOL 75 mL/100 mL
INACTIVE INGREDIENTS: .ALPHA.-TOCOPHEROL; WATER; TROLAMINE; ALOE VERA LEAF; GLYCERIN; CARBOMER HOMOPOLYMER, UNSPECIFIED TYPE

Active Ingredient

Ethyl Alcohol 75.0%

Purpose

Antimicrobial

Uses

- for handwashing to decrease bacteria on the skin
- recommended for repeated use

Warnings

For external use only

Flammable, keep away from heat and flame

Do not use in the eyes. In case of contact, rinse eyes thoroughly with water.

Stop use and ask a doctor if irritation and redness develop and persist for more than 72 hours.

KEEP OUT OF REACH OF CHILDREN

If swallowed, get medical help or contact a Posion Control Center right away.

Directions

- wet hands thoroughly with product briskly rub hands together until dry
- supervise children under 6 years in the use of this product

Other information

- store at 20C to 25C (68 to 77F)
- may discolor certain fabrics.

Inactive ingredient

Water

Glycerin

Carbomer

Aloe Vera

triethanolamine

Vitamin E